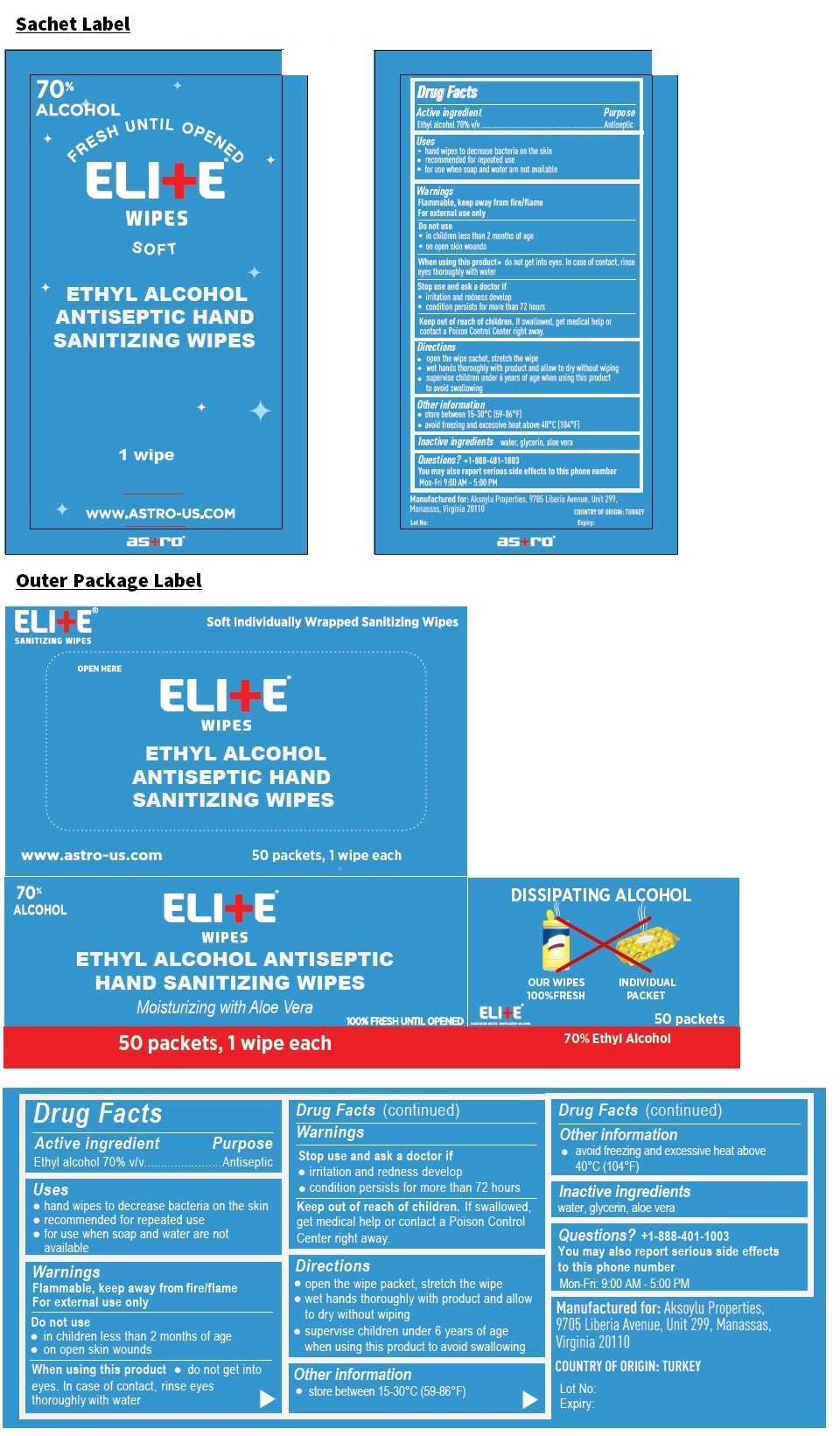 DRUG LABEL: ELITE WIPES
NDC: 81682-001 | Form: CLOTH
Manufacturer: PROKIM KAGITCILIK VE KIMYEVI MADDELER LIMITED SIRKETI
Category: otc | Type: HUMAN OTC DRUG LABEL
Date: 20210401

ACTIVE INGREDIENTS: ALCOHOL 70 mL/100 mL
INACTIVE INGREDIENTS: WATER; GLYCERIN; ALOE VERA LEAF

ELI+E® WIPES

Active ingredient

Ethyl alcohol 70% v/v

Purpose

Antiseptic

Uses

• hand wipes to decrease bacteria on the skin
• recommended for repeated use
• for use when soap and water are not available

Warnings

Flammable, keep away from fire/flame
For external use only

Do not use
• in children less than 2 months of age
• on open skin wounds

When using this product • do not get into eyes. In case of contact, rinse eyes thoroughly with water

Stop use and ask a doctor if
• irritation and redness develop
• condition persists for more than 72 hours

Keep out of reach of children. If swallowed, get medical help or contact a Poison Control Center right away.

Directions

• open the wipe sachet, stretch the wipe
• wet hands thoroughly with product and allow to dry without wiping
• supervise children under 6 years of age when using this product to avoid swallowing

Other information

• store between 15-30°C (59-86°F)
• avoid freezing and excessive heat above 40°C (104°F)

Inactive ingredients

water, glycerin, aloe vera

Questions? +1-888-401-1003

You may also report serious side effects to this phone number
Mon-Fri 9:00 AM - 5:00 PM

70% ALCOHOL

ETHYL ALCOHOL ANTISEPTIC HAND SANITIZING WIPES

Moisturizing with Aloe Vera

100% FRESH UNTIL OPENED

DISSIPATING ALCOHOL

OUR WIPES 100%FRESH

INDIVIDUAL PACKET

Soft Individually Wrapped Sanitizing Wipes

www.astro-us.com

Manufactured for: Aksoylu Properties, 9705 Liberia Avenue, Unit 299, Manassas, Virginia 20110

COUNTRY OF ORIGIN: TURKEY
astro®